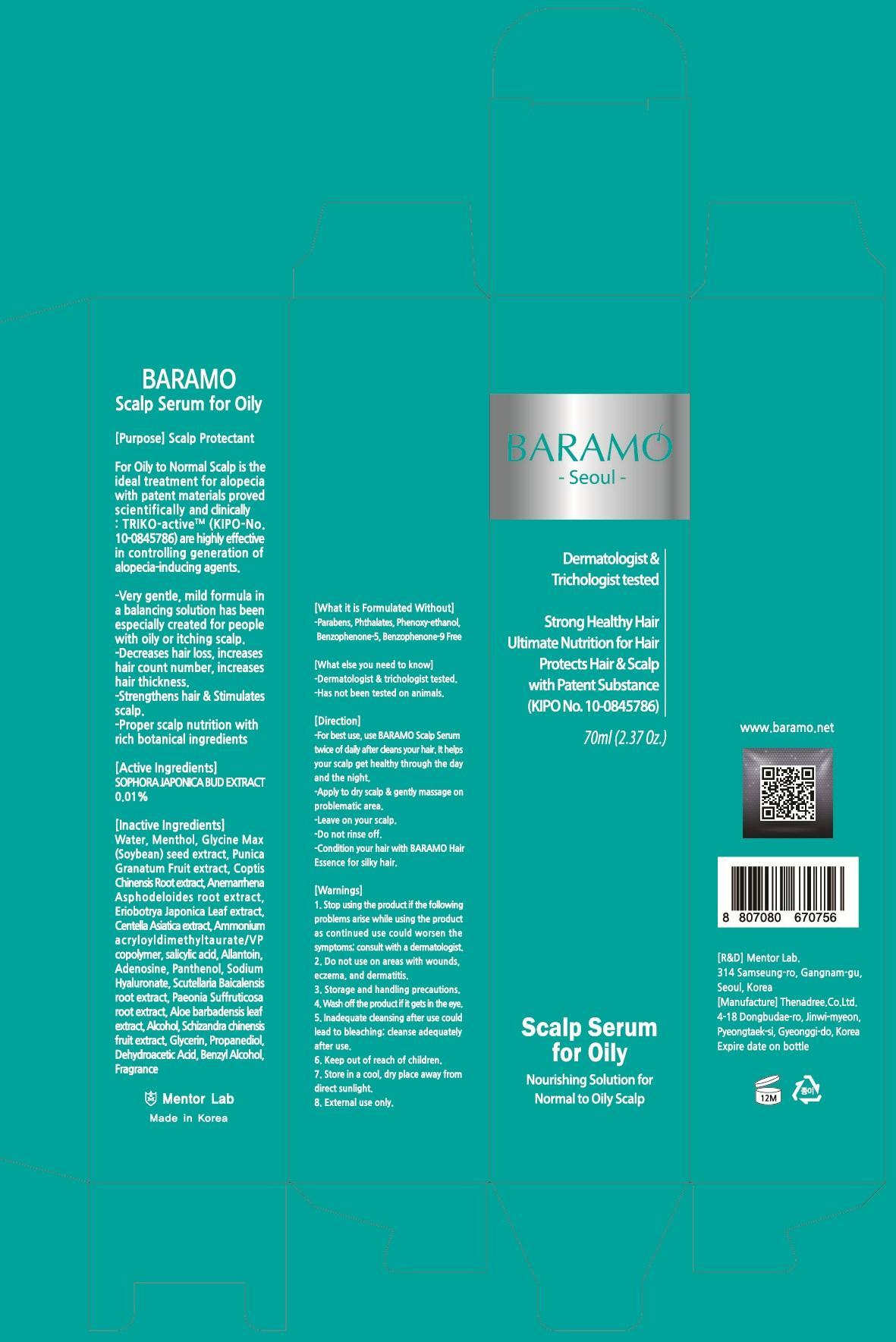 DRUG LABEL: BARAMO SCALP SERUM
NDC: 69961-020 | Form: SOLUTION
Manufacturer: Mentor Lab
Category: otc | Type: HUMAN OTC DRUG LABEL
Date: 20150806

ACTIVE INGREDIENTS: STYPHNOLOBIUM JAPONICUM FLOWER BUD 0.07 mg/70 mL
INACTIVE INGREDIENTS: Water; Menthol

ACTIVE INGREDIENT

Active Ingredients: SOPHORA JAPONICA BUD EXTRACT 0.01%

INACTIVE INGREDIENT

Inactive Ingredients: Water, Menthol, Glycine Max(Soybean) seed extract, Punica Granatum Fruit extract, Coptis Chinensis Root extract, Anemarrhena Asphodeloides root extract, Eriobotrya Japonica Leaf extract, Centella Asiatica extract, Ammonium acryloyldimethyltaurate/VP copolymer, salicylic acid, Allantoin, Adenosine, Panthenol, Sodium Hyaluronate, Scutellaria Baicalensis root extract, Paeonia Suffruticosa root extract, Aloe barbadensis leaf extract, Alcohol, Schizandra chinensis fruit extract, Glycerin, Propanediol, Dehydroacetic Acid, Benzyl Alcohol, Fragrance

PURPOSE

Propose: Scalp Protectant

WARNINGS

Warnings: 1. Stop using the product if the following problems arise while using the product as continued use could worsen the symptoms; consult with a dermatologist. 2. Do not use on areas with wounds, eczema, and dermatitis. 3. Storage and handling precautions. 4. Wash off the product if it gets in the eye. 5. Inadequate cleansing after use could lead to bleaching; cleanse adequately after use. 6. Keep out of reach of children. 7. Store in a cool, dry place away from direct sunlight. 8. External use only.

KEEP OUT OF REACH OF CHILDREN

Direction

-For best use, use BARAMO Scalp Serum twice of daily after cleans your hair. It helps your scalp get healthy through the day and the night.

-Apply to dry scalp & gently massage on problematic area.

-Leave on your scalp.

-Do not rinse off.

-Condition your hair with BARAMO Hair Essence for silky hair.

Direction

-For best use, use BARAMO Scalp Serum twice of daily after cleans your hair. It helps your scalp get healthy through the day and the night.

-Apply to dry scalp & gently massage on problematic area.

-Leave on your scalp.

-Do not rinse off.

-Condition your hair with BARAMO Hair Essence for silky hair.